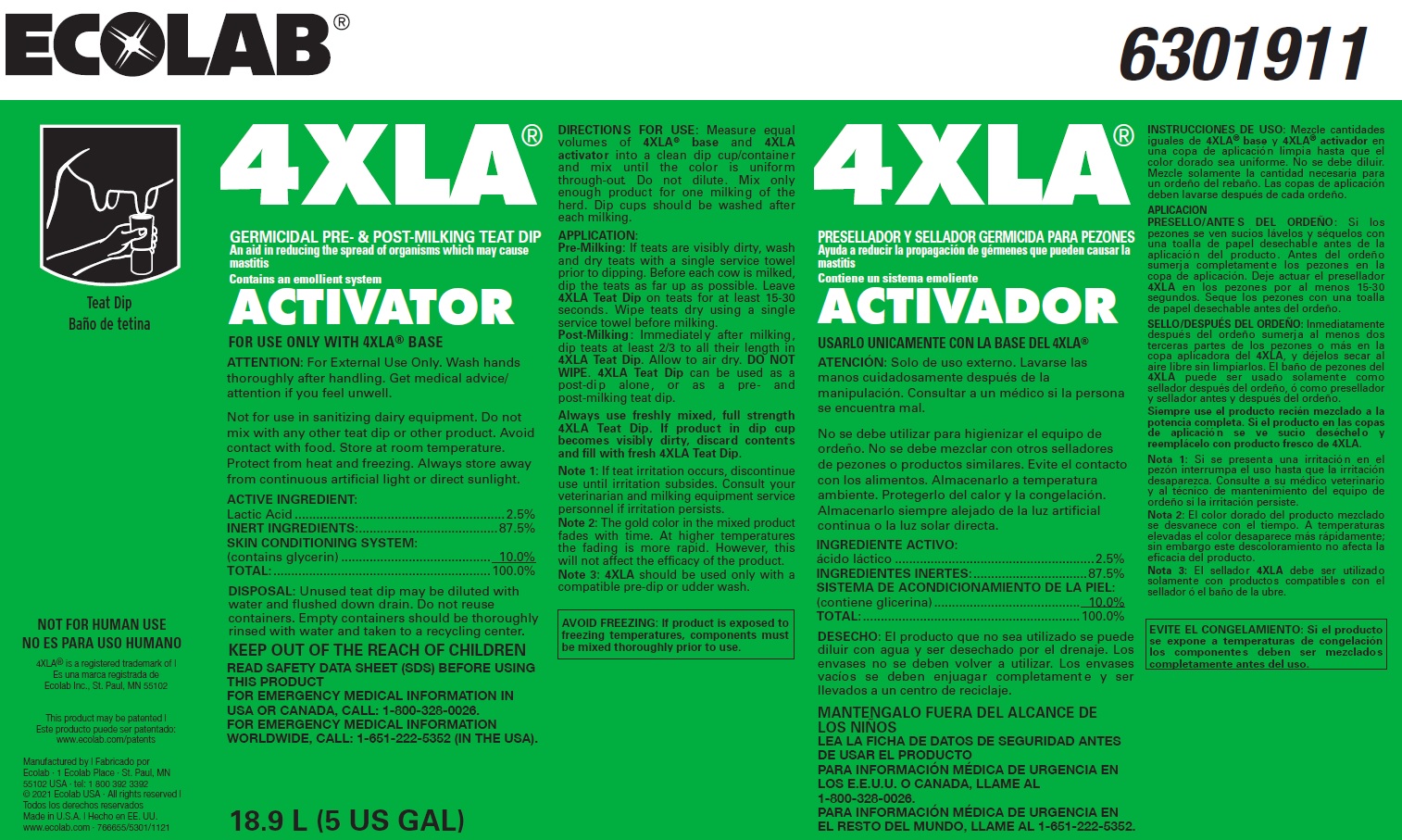 DRUG LABEL: 4XLA
NDC: 47593-424 | Form: SOLUTION
Manufacturer: Ecolab Inc.
Category: animal | Type: OTC ANIMAL DRUG LABEL
Date: 20250808

ACTIVE INGREDIENTS: LACTIC ACID 25 mg/1 mL
INACTIVE INGREDIENTS: WATER; GLYCERIN; ISOPROPYL ALCOHOL

SAFE HANDLING WARNING

ATTENTION: For External Use Only. Wash hands thoroughly after handling. Get medical advice/ attention if you feel unwell.

DISPOSAL: Unused teat dip may be diluted with water and flushed down drain. Do not reuse containers. Empty containers should be thoroughly rinsed with water and taken to a recycling center.

VETERINARY INDICATIONS

DIRECTIONS FOR USE: Measure equal volume s of 4XLA® base and 4XLA activator into a clean dip cup/container and mix until the color is uniform through-out. Do not dilute. Mix only enough product for one milking of the herd. Dip cups should be washed after each milking.

APPLICATION:

Pre-Milking: If teats are visibly dirty, wash and dry teats with a single service towel prior to dipping. Before each cow is milked, dip the teats as far up as possible. Leave 4XLA Teat Dip on teats for at least 15-30 seconds. Wipe teats dry using a single service towel before milking.

Post-Milking: Immediately after milking, dip teats at least 2/3 to all their length in 4XLA Teat Dip. Allow to air dry. DO NOT WIPE. 4XLA Teat Dip can be used as a post-di p alone, or as a pre- and post-milking teat dip.

Always use freshly mixed, full strength 4XLA Teat Dip. If product in dip cup becomes visibly dirty, discard contents and fill with fresh 4XLA Teat Dip.

Note 1: If teat irritation occurs, discontinue use until irritation subsides. Consult your veterinarian and milking equipment service personnel if irritation persists.

Note 2: The gold color in the mixed product fades with time. At higher temperatures the fading is more rapid. However, this will not affect the efficacy of the product. Note 3: 4XLA should be used only with a compatible pre-dip or udder wash.

OTHER SAFETY INFORMATION

Not for use in sanitizing dairy equipment. Do not mix with any other teat dip or other product. Avoid contact with food. Store at room temperature. Protect from heat and freezing. Always store away from continuous artificial light or direct sunlight.

KEEP OUT OF THE REACH OF CHILDREN

READ SAFETY DATA SHEET (SDS) BEFORE USING THIS PRODUCT

FOR EMERGENCY MEDICAL INFORMATION IN USA OR CANADA, CALL: 1-800-328-0026.

FOR EMERGENCY MEDICAL INFORMATION WORLDWIDE, CALL: 1-651-222-5352 (IN THE USA).

AVOID FREEZING: If product is exposed to freezing temperatures, components must be mixed thoroughly prior to use.

NOT FOR HUMAN USE

Principal display panel and representative container

4XLA 6301911

GERMICIDAL PRE- & POST-MILKING TEAT DIP

An aid in reducing the spread of organisms which may cause mastitis

Contains an emollient system

ACTIVATOR

FOR USE ONLY WITH 4XLA® BASE

ACTIVE INGREDIENT:

Lactic Acid ...........................................................2.5%

INERT INGREDIENTS:.......................................87.5%

SKIN CONDITIONING SYSTEM:

(contains glycerin) .......................................... 10.0%

TOTAL:.............................................................100.0%

Manufactured by | Ecolab · 1 Ecolab Place · St. Paul, MN 55102 USA · tel: 1 800 392 3392

© 2021 Ecolab USA · All rights reserved

Made in U.S.A. | www.ecolab.com · 766655/5301/1121